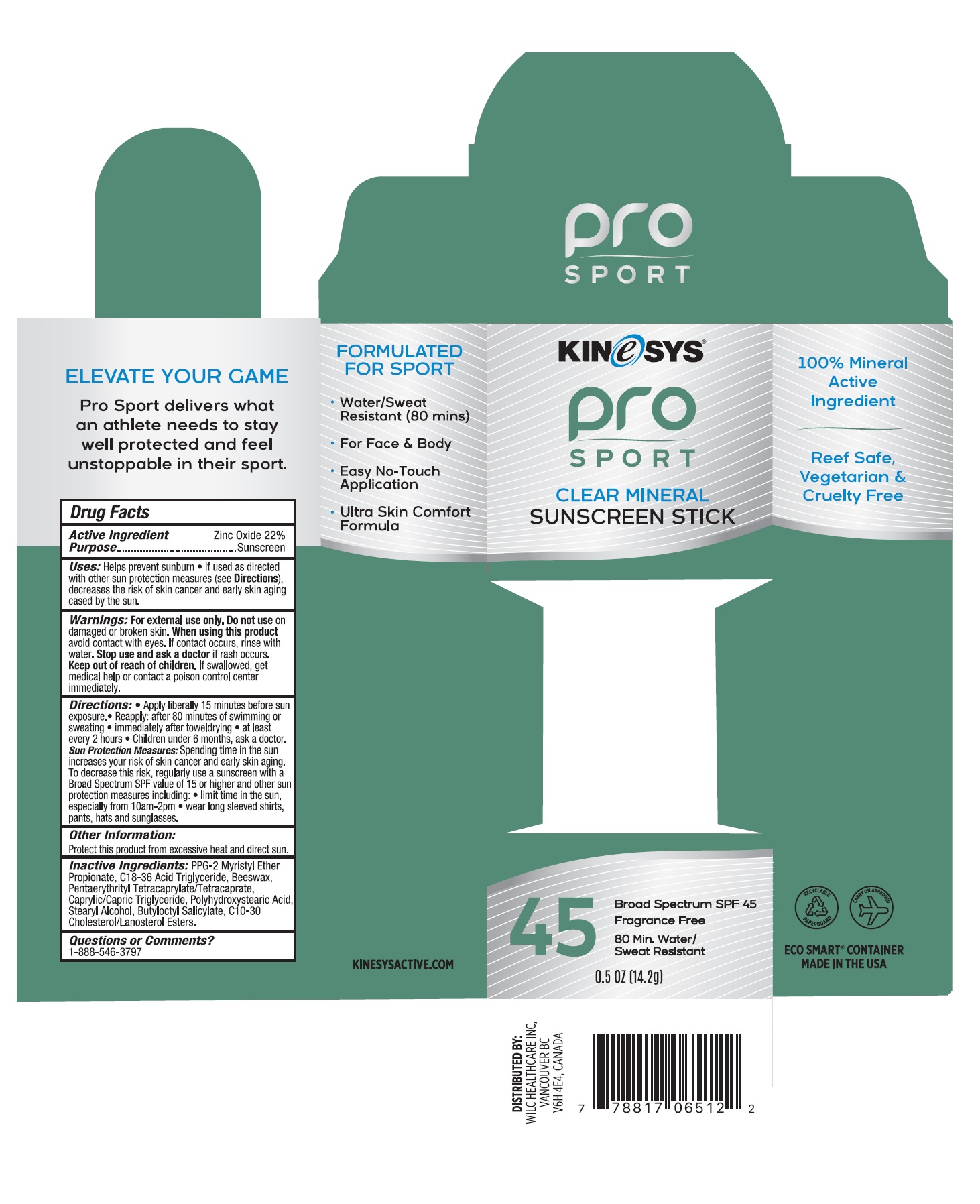 DRUG LABEL: KINeSYS Pro Sport Clear Mineral Sunscreen Stick Broad Spectrum SPF45
NDC: 61481-3008 | Form: STICK
Manufacturer: Wilc Healthcare Inc
Category: otc | Type: HUMAN OTC DRUG LABEL
Date: 20251010

ACTIVE INGREDIENTS: ZINC OXIDE 22 g/100 g
INACTIVE INGREDIENTS: C18-36 ACID TRIGLYCERIDE; PPG-2 MYRISTYL ETHER PROPIONATE; WHITE WAX; MEDIUM-CHAIN TRIGLYCERIDES; STEARYL ALCOHOL; PENTAERYTHRITYL TETRACAPRYLATE/TETRACAPRATE; BUTYLOCTYL SALICYLATE; POLYHYDROXYSTEARIC ACID (2300 MW); C10-30 CHOLESTEROL/LANOSTEROL ESTERS

Active Ingredient

Zinc Oxide 22%

Purpose

Sunscreen

Uses

- helps prevent sunburn
- if used as directed with other sun protection measures (see Directions), decreases the risk of skin cancer and early skin aging cased by the sun.

Warnings

For external use only
Do not useon damaged or broken skin.
When using this productavoid contact with eyes. If contact occurs, rinse with water.
Stop use and ask a doctor ifrash occurs.
Keep out of reach of children. If swallowed, get medical help or contact a poison control center immediately.

Directions

Apply liberally 15 minutes before sun exposure

Reapply: after 8o minutes of swimming or sweating

- immediately after towel drying
- at least every 2 hours
- Children under 6 months, ask a doctor.

Sun Protection Measures: Spending time in the sun increases your risk of skin cancer and early skin aging. To decrease this risk, regularly use a sunscreen with a Broad Spectrum SPF value of 15 or higher and other sun protection measures including:

- limit time in the sun, especially from 10am-2pm
- wear long sleeved shirts, pants, hats and sunglasses.

Other Information

Protect this product from excessive heat and direact sun

Inactive Ingredients

PPG-2 Myristyl Ether Propionate, C18-36 Acid Triglyceride, Beeswax, Pentaerythrityl Tetracaprylate /Tetracaprate, Caprylic/Capric Triglyceride, Polyhydroxystearic Acid, Stearyl Alcohol, Butyloctyl Salicylate, C10-30 Cholesterol/Lanosterol Esters

Question or Comments?

1-888-546-3797